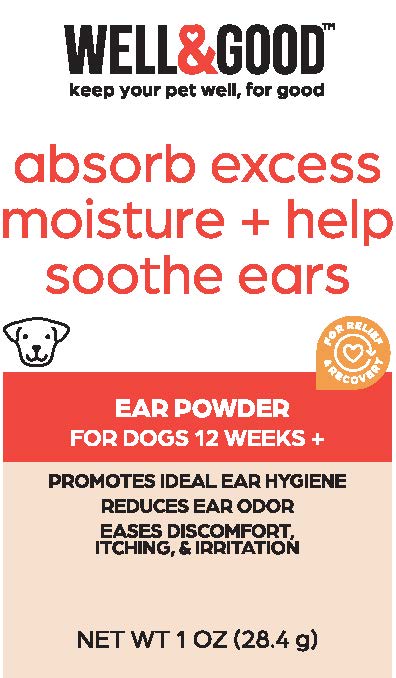 DRUG LABEL: Well and Good Relieve Ear Powder
NDC: 77720-032 | Form: POWDER
Manufacturer: Skaffles Group Limited Liability Company
Category: animal | Type: OTC ANIMAL DRUG LABEL
Date: 20220916

ACTIVE INGREDIENTS: ZINC OXIDE 6 g/100 g
INACTIVE INGREDIENTS: TALC; BENTONITE; HAMAMELIS VIRGINIANA LEAF; ROSEMARY

Ear Powder

INDICATIONS AND USAGE

The WELL & GOOD EAR
POWDER helps absorb harmful
excess moisture, making ears
easier to clean. This gentle
formula uses rosemary extract
to also relieve itching and
irritation in your dog's ears.

WARNINGS AND PRECAUTIONS

CAUTION: FOR PET USE ONLY. Keep out of
reach of children. In case of accidental
consumption, contact a health care
professional immediately. In case of eye
contact, rinse thoroughly with water. If there
is any irritation, discontinue use and seek
veterinary care.

For use on dogs 12 weeks or older

DO NOT USE IF PRODUCT APPEARS TO BE

TAMPERED WITH OR SEAL IS BROKEN.

STORE PRODUCT IN COOL PLACE. DO NOT

EXPOSE TO EXCESSIVE HEAT OR MOISTURE.

INSTRUCTIONS:

Expose ear canal and hold applicator tip 1 inch from canal opening.
Squeeze a small amount of ear powder directly into the canal.
Gently massage powder into hair and skin.

If removing hair, carefully grip hair at the root and tug to remove.

Use regularly with ear cleaning wipes or ear cleaning liquid to help keep ears healthy, clean, and dry.

Principal Display Panel

WELL&GOOD™
keep your pet well, for good

absorb excess moisture + helps soothe ears

For Relief & Recovery

EAR POWDER FOR DOGS 12 WEEKS+

PROMOTES IDEAL EAR HYGIENE
REDUCES EAR ODOR
EASES DISCOMFORT, ITCHING, & IRRITATION

NET WT 1 OZ (28.4g)

Ingredients

Talc, Bentonite, Zinc Oxide, Hamamelis Virginiana Leaf, Rosemary Extract.

Distributed by: International Pet Supplies and Distribution, Inc., San Diego, CA 92127

Contact us at 1.855.FAQ.Petco

©2022 Petco Animal Supplies, Inc.

All Rights Reserved. Made in China